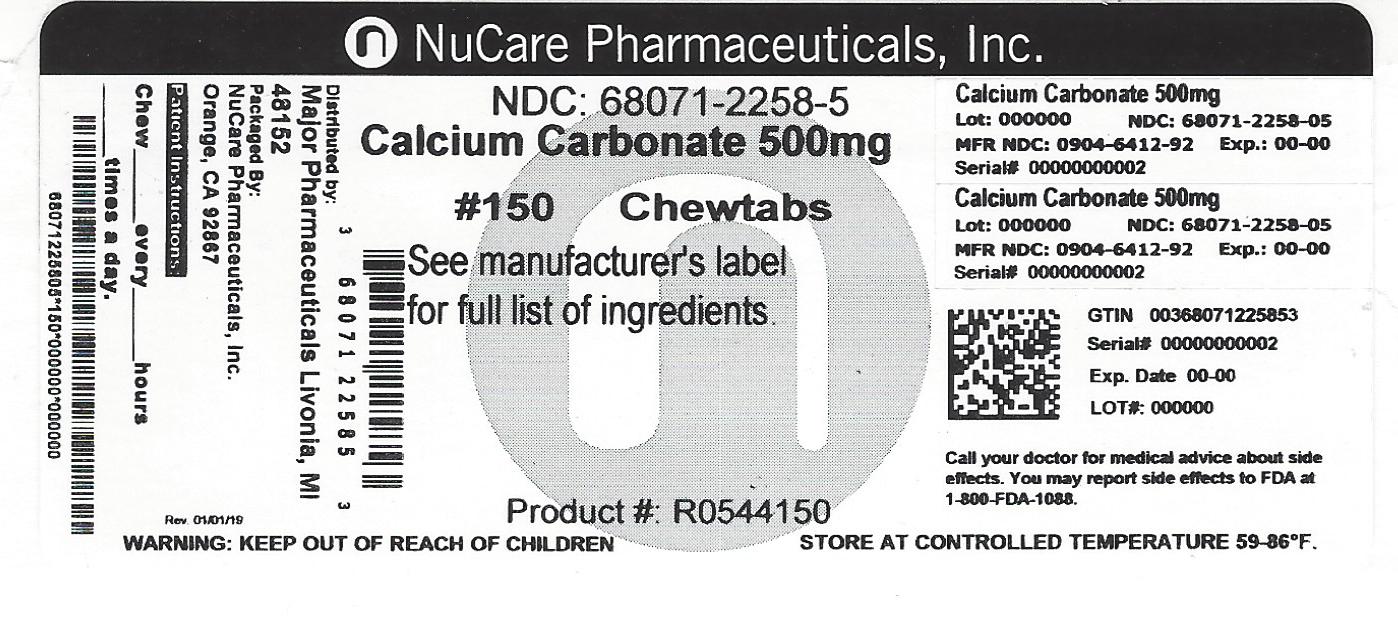 DRUG LABEL: Calcium Carbonate
NDC: 68071-2258 | Form: TABLET, CHEWABLE
Manufacturer: NuCare Pharmaceuticals,Inc.
Category: otc | Type: HUMAN OTC DRUG LABEL
Date: 20240717

ACTIVE INGREDIENTS: CALCIUM CARBONATE 500 mg/1 1
INACTIVE INGREDIENTS: ADIPIC ACID; D&C RED NO. 27; D&C YELLOW NO. 10; DEXTROSE, UNSPECIFIED FORM; FD&C BLUE NO. 1; FD&C YELLOW NO. 6; MAGNESIUM STEARATE; MALTODEXTRIN; STARCH, CORN; SUCRALOSE

Major Regular Strength Antacid 150 Chewable Tablets

Active ingredient

Calcium Carbonate USP 500mg

Purpose

Antacid

Uses

relieves:

• heartburn

• sour stomach

• acid indigestion

• upset stomach associated with these symptoms

Warnings

Ask a doctor or pharmacist before use if you are presently taking a prescription drug. Antacids may interact with certain prescription drugs.

When using this product

- do not take more than 15 tablets in 24 hours
- If pregnant do not take more than 10 tablets in 24 hours
- do not use the maximum dosage for more than 2 weeks except under the advice and supervision of a doctor.

Directions

- Adults and children 12 years of age and over: chew 2-4 tablets as symptoms occur, or as directed by a doctor.
- Do not take for symptoms that persist for more than 2 weeks unless advised by a doctor.

Other Information

- each tablet contains: elemental calcium 200 mg
- Store at room temperature. Keep the container tightly closed

Safety sealed: Do not use if printed seal under cap is torn or missing.

Inactive ingredients

adipic acid, D&C Red No. 27 Lake, D&C Yellow No. 10 Lake, dextrose, FD&C Blue No. 1 Lake, FD&C Yellow No. 6 Lake, flavors, magnesium stearate, maltodextrin, starch, sucralose.